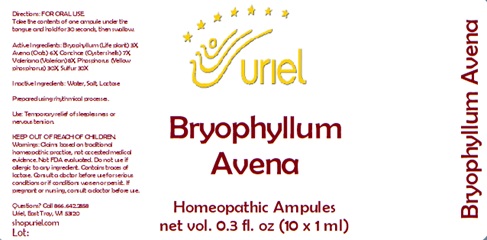 DRUG LABEL: Bryophyllum Avena
NDC: 48951-2090 | Form: LIQUID
Manufacturer: Uriel Pharmacy Inc.
Category: homeopathic | Type: HUMAN OTC DRUG LABEL
Date: 20241206

ACTIVE INGREDIENTS: KALANCHOE DAIGREMONTIANA LEAF 3 [hp_X]/1 mL; AVENA SATIVA FLOWERING TOP 6 [hp_X]/1 mL; OSTREA EDULIS SHELL 7 [hp_X]/1 mL; VALERIAN 8 [hp_X]/1 mL; PHOSPHORUS 30 [hp_X]/1 mL; SULFUR 30 [hp_X]/1 mL
INACTIVE INGREDIENTS: WATER; SODIUM CHLORIDE; LACTOSE

Bryophyllum Avena

INDICATIONS AND USAGE

Directions: FOR ORAL USE.

DOSAGE AND ADMINISTRATION

Take the contents of one ampule under the tongue and hold for 30 seconds, then swallow.

ACTIVE INGREDIENT

Active Ingredients: Bryophyllum (Life plant) 3X, Avena (Oats) 6X, Conchae (Oyster shells)7X, Valeriana (Valerian) 8X, Phosphorus (Yellow phosphorus) 30X, Sulfur 30X

Inactive Ingredients: Water, Salt, Lactose

Prepared using rhythmical processes.

PURPOSE

Use: Temporary relief of sleeplessness or nervous tension.

KEEP OUT OF REACH OF CHILDREN.

WARNINGS

Warnings: Claims based on traditional homeopathic practice, not accepted medical evidence. Not FDA evaluated. Do not use if allergic to any ingredient. Contains traces of lactose. Consult a doctor before use for serious conditions or if conditions worsen or persist. If pregnant or nursing, consult a doctor before use.

QUESTIONS

Questions? Call 866.642.2858 Uriel, East Troy, WI 53120 shopuriel.com Lot: